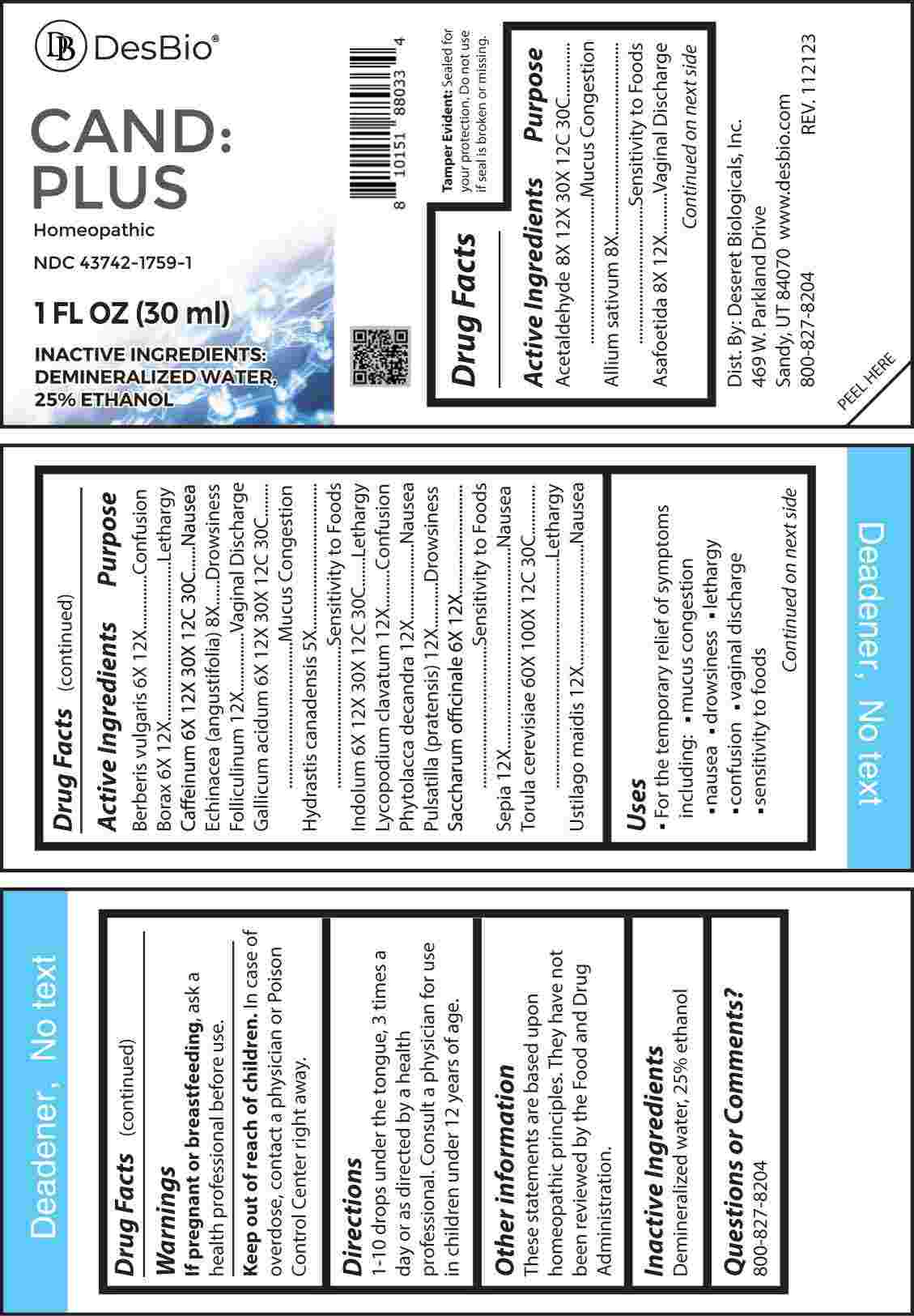 DRUG LABEL: Cand Plus
NDC: 43742-1759 | Form: LIQUID
Manufacturer: Deseret Biologicals, Inc.
Category: homeopathic | Type: HUMAN OTC DRUG LABEL
Date: 20240306

ACTIVE INGREDIENTS: GOLDENSEAL 5 [hp_X]/1 mL; BERBERIS VULGARIS ROOT BARK 6 [hp_X]/1 mL; SODIUM BORATE 6 [hp_X]/1 mL; SUCROSE 6 [hp_X]/1 mL; CAFFEINE 6 [hp_X]/1 mL; GALLIC ACID MONOHYDRATE 6 [hp_X]/1 mL; INDOLE 6 [hp_X]/1 mL; GARLIC 8 [hp_X]/1 mL; ECHINACEA ANGUSTIFOLIA WHOLE 8 [hp_X]/1 mL; FERULA ASSA-FOETIDA RESIN 8 [hp_X]/1 mL; ACETALDEHYDE 8 [hp_X]/1 mL; ESTRONE 12 [hp_X]/1 mL; LYCOPODIUM CLAVATUM SPORE 12 [hp_X]/1 mL; PHYTOLACCA AMERICANA ROOT 12 [hp_X]/1 mL; PULSATILLA PRATENSIS WHOLE 12 [hp_X]/1 mL; SEPIA OFFICINALIS JUICE 12 [hp_X]/1 mL; USTILAGO MAYDIS 12 [hp_X]/1 mL; SACCHAROMYCES CEREVISIAE 60 [hp_X]/1 mL
INACTIVE INGREDIENTS: WATER; ALCOHOL

DRUG FACTS:

ACTIVE INGREDIENTS:

Acetaldehyde 8X, 12X, 30X, 12C, 30C, Allium Sativum 8X, Asafoetida 8X, 12X, Berberis Vulgaris 6X, 12X, Borax 6X, 12X, Caffeinum 6X, 12X, 30X, 12C, 30C, Echinacea (Angustifolia) 8X, Folliculinum 12X, Gallicum Acidum 6X, 12X, 30X, 12C, 30C, Hydrastis Canadensis 5X, Indolum 6X, 12X, 30X, 12C, 30C, Lycopodium Clavatum 12X, Phytolacca Decandra 12X, Pulsatilla (Pratensis) 12X, Saccharum Officinale 6X, 12X, Sepia 12X, Torula Cerevisiae 60X, 100X, 12C, 30C, Ustilago Maidis 12X.

PURPOSE:

Acetaldehyde – Mucus Congestion, Allium Sativum – Sensitivity to Foods, Asafoetida – Vaginal Discharge, Berberis Vulgaris - Confusion, Borax - Lethargy, Caffeinum - Nausea, Echinacea Angustifolia - Drowsiness, Folliculinum – Vaginal Discharge, Gallicum Acidum – Mucus Congestion, Hydrastis Canadensis – Sensitivity to Foods, Indolum - Lethargy, Lycopodium Clavatum - Confusion, Phytolacca Decandra - Nausea, Pulsatilla Pratensis - Drowsiness, Saccharum Officinale – Sensitivity to Foods, Sepia - Nausea, Torula Cerevisiae - Lethargy, Ustilago Maidis - Nausea

USES:

• For the temporary relief of symptoms including:

• mucous congestion • nausea

• drowsiness • lethargy

• confusion • vaginal discharge

• sensitivity to foods

These statements are based upon homeopathic principles. They have not been reviewed by the Food and Drug Administration.

WARNINGS:

If pregnant or breast-feeding, ask a health professional before use.

Keep out of reach of children. In case of overdose, contact a physician or Poison Control Center right away.

Tamper Evident: Sealed for your protection. Do not use if seal is broken or missing.

KEEP OUT OF REACH OF CHILDREN:

In case of overdose, contact a physician or Poison Control Center right away.

DIRECTIONS:

1-10 drops under the tongue, 3 times a day or as directed by a health professional. Consult a physician for use in children under 12 years of age.

INACTIVE INGREDIENTS:

Demineralized water, 25% ethanol

QUESTIONS:

Dist. By: Deseret Biologicals, Inc.
469 W. Parkland Drive
Sandy, UT 84070

www.desbio.com

800-827-8204

PACKAGE LABEL DISPLAY:

Des Bio

CAND:PLUS

Homeopathic

NDC 43742-1759-1

1 FL OZ (30 ml)